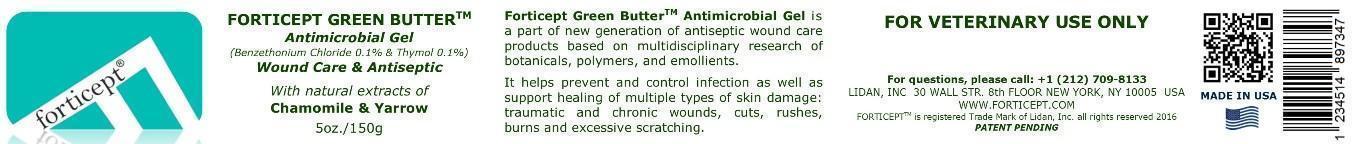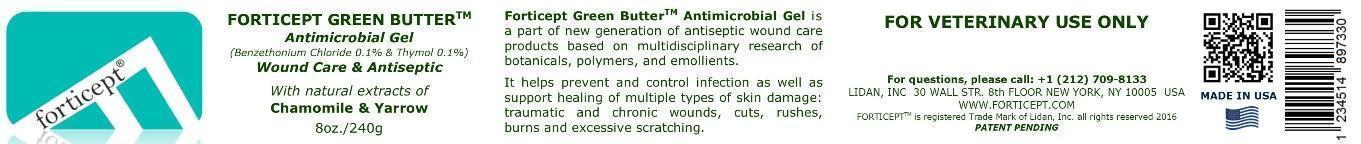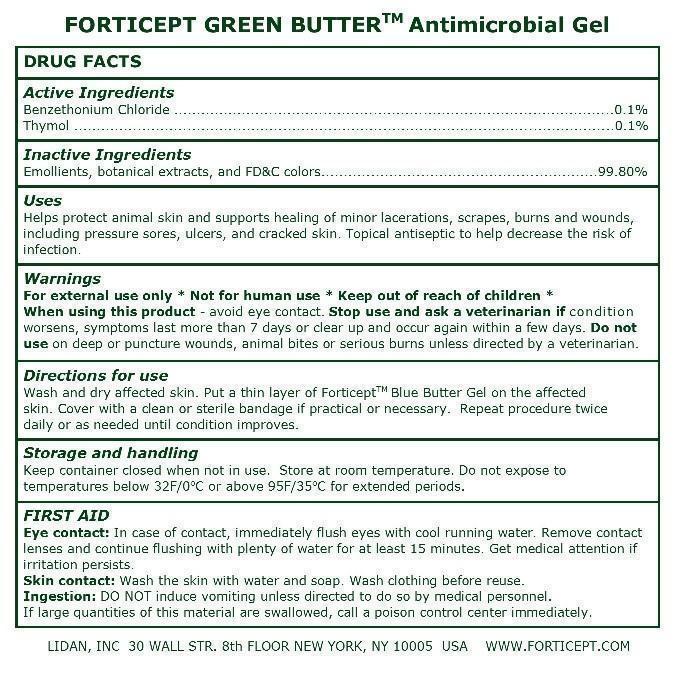 DRUG LABEL: Forticept Green Butter Antimicrobial Gel
NDC: 52261-0703 | Form: Gel
Manufacturer: Cosco International, Inc.
Category: animal | Type: OTC ANIMAL DRUG LABEL
Date: 20161130

ACTIVE INGREDIENTS: benzethonium chloride 1 g/1000 g; thymol 1 g/1000 g

Active Ingredients

Benzethonium Chloride .................................................................................................0.1% Thymol .......................................................................................................................0.1%

Inactive ingredients:

Emollients, botanical extracts, and FD&C colors.............................................................99.8%

Uses

For external use only * Not for human use * Keep out of reach of children *

When using this product - avoid eye contact. Stop use and ask a veterinarian if condition worsens, symptoms last more than 7 days or clear up and occur again within a few days. Do not use on deep or puncture wounds, animal bites or serious burns unless directed by a veterinarian.

Warnings

For external use only * Not for human use * Keep out of reach of children * When using this product - avoid eye contact. Stop use and ask a veterinarian if condition worsens, symptoms last more than 7 days or clear up and occur again within a few days. Do not use on deep or puncture wounds, animal bites or serious burns unless directed by a veterinarian.

Directions for use

Wash and dry affected skin. Put a thin layer of ForticeptTM Blue Butter Gel on the affected skin. Cover with a clean or sterile bandage if practical or necessary. Repeat procedure twice daily or as needed until condition improves.

Storage and handling

Keep container closed when not in use. Store at room temperature. Do not expose to temperatures below 32F/0oC or above 95F/35oC for extended periods.

FIRST AID

Eye contact: In case of contact, immediately flush eyes with cool running water. Remove contact lenses and continue flushing with plenty of water for at least 15 minutes. Get medical attention if irritation persists.

Skin contact: Wash the skin with water and soap. Wash clothing before reuse.

Ingestion: DO NOT induce vomiting unless directed to do so by medical personnel. If large quantities of this material are swallowed, call a poison control center immediately.